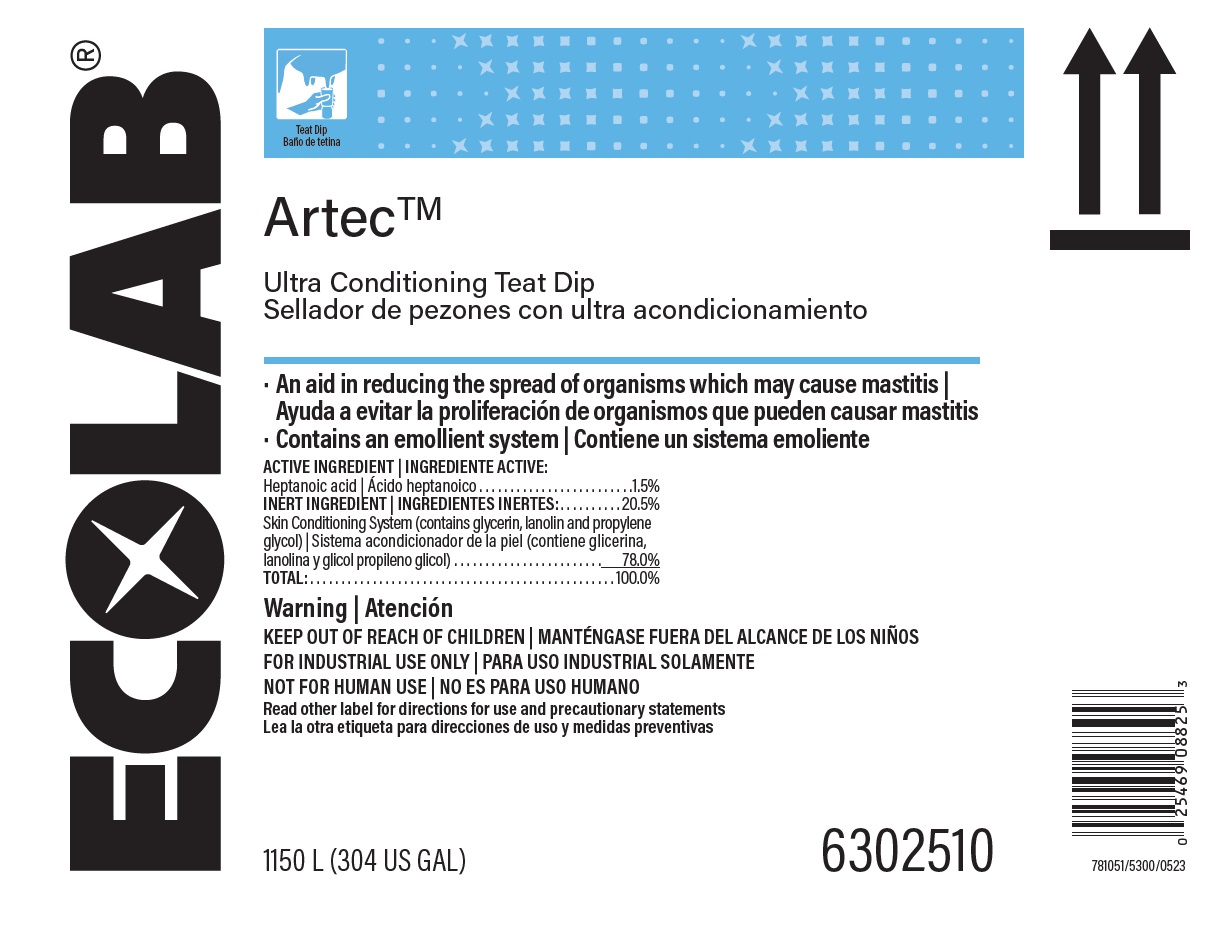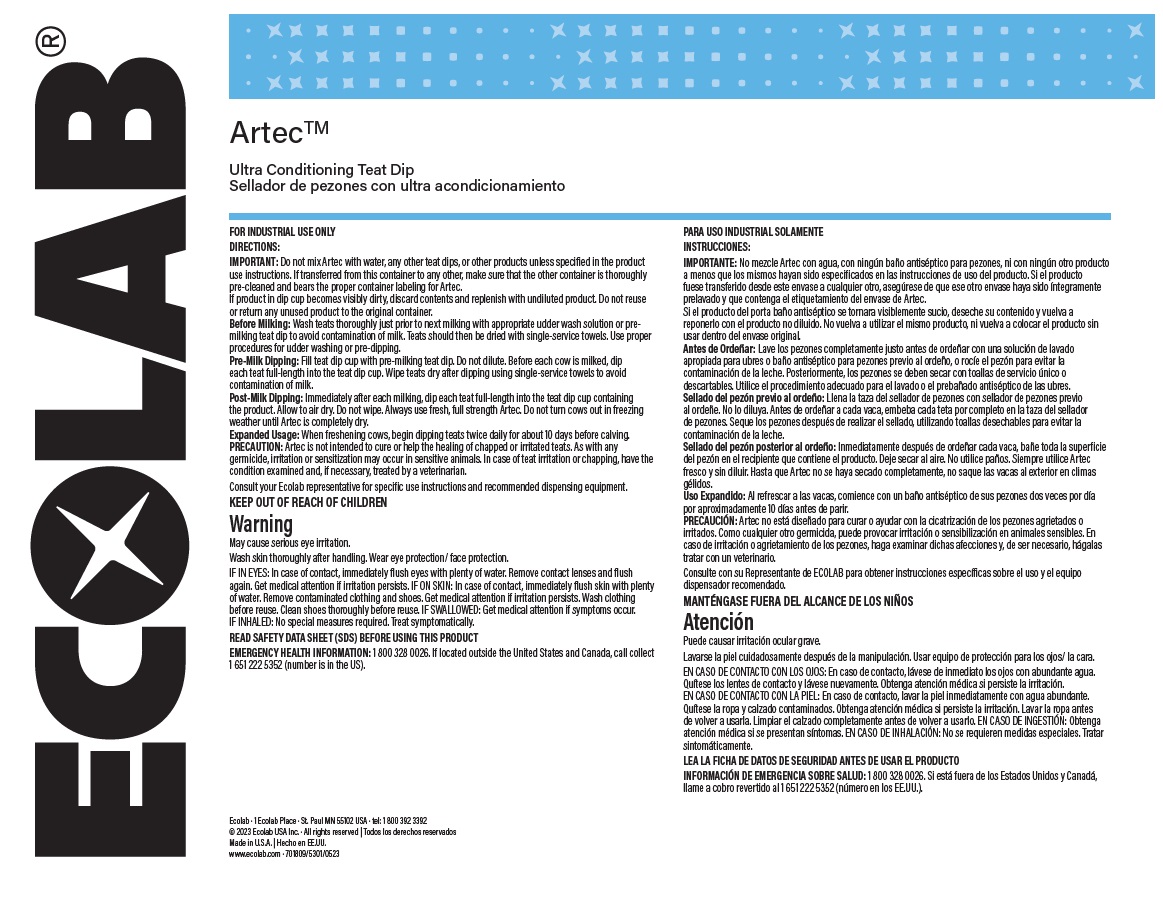 DRUG LABEL: Artec
NDC: 47593-346 | Form: SOLUTION
Manufacturer: Ecolab Inc.
Category: animal | Type: OTC ANIMAL DRUG LABEL
Date: 20250804

ACTIVE INGREDIENTS: HEPTANOIC ACID 15000 mg/1 L
INACTIVE INGREDIENTS: WATER; PROPYLENE GLYCOL; GLYCERIN; PEG-75 LANOLIN

Warning

KEEP OUT OF REACH OF CHILDREN

FOR INDUSTRIAL USE ONLY

NOT FOR HUMAN USE

Read other label for directions for use and precautionary statements

DIRECTIONS:

IMPORTANT: Do not mix Artec with water, any other teat dips, or other products unless specified in the product use instructions. If transferred from this container to any other, make sure that the other container is thoroughly pre-cleaned and bears the proper container labeling for Artec.

If product in dip cup becomes visibly dirty, discard contents and replenish with undiluted product. Do not reuse or return any unused product to the original container.

Before Milking: Wash teats thoroughly just prior to next milking with appropriate udder wash solution or pre-milking teat dip to avoid contamination of milk. Teats should then be dried with single-service towels. Use proper procedures for udder washing or pre-dipping.

Pre-Milk Dipping: Fill teat dip cup with pre-milking teat dip. Do not dilute. Before each cow is milked, dip

each teat full-length into the teat dip cup. Wipe teats dry after dipping using single-service towels to avoid contamination of milk.

Post-Milk Dipping: Immediately after each milking, dip each teat full-length into the teat dip cup containing the product. Allow to air dry. Do not wipe. Always use fresh, full strength Artec. Do not turn cows out in freezing weather until Artec is completely dry.

Expanded Usage: When freshening cows, begin dipping teats twice daily for about 10 days before calving. PRECAUTION: Artec is not intended to cure or help the healing of chapped or irritated teats. As with any germicide, irritation or sensitization may occur in sensitive animals. In case of teat irritation or chapping, have the condition examined and, if necessary, treated by a veterinarian.

Consult your Ecolab representative for specific use instructions and recommended dispensing equipment.

KEEP OUT OF REACH OF CHILDREN

Warning

May cause serious eye irritation.

Wash skin thoroughly after handling. Wear eye protection/ face protection.

IF IN EYES: In case of contact, immediately flush eyes with plenty of water. Remove contact lenses and flush again. Get medical attention if irritation persists. IF ON SKIN: In case of contact, immediately flush skin with plenty of water. Remove contaminated clothing and shoes. Get medical attention if irritation persists. Wash clothing before reuse. Clean shoes thoroughly before reuse. IF SWALLOWED: Get medical attention if symptoms occur. IF INHALED: No special measures required. Treat symptomatically.

READ SAFETY DATA SHEET (SDS) BEFORE USING THIS PRODUCT

EMERGENCY HEALTH INFORMATION: 1 800 328 0026. If located outside the United States and Canada, call collect 1 651 222 5352 (number is in the US).

Principal Display panel and representative container

Artec

Ultra Conditioning Teat Dip

An aid in reducing the spread of organisms which may cause mastitis

Contains and emollient system

ACTIVE INGREDIENT

Heptanoic acid: …………………………1.5%

INERT INGREDIENT: ……………………..20.5%

Skin Conditioning System (contains glycerin, lanolin and propylene glycol)…78.0%

TOTAL: 100.0%

Warning

KEEP OUT OF REACH OF CHILDREN

FOR INDUSTRIAL USE ONLY

NOT FOR HUMAN USE

Read other label for directions for use and precautionary statements

1150 L (304 US GAL)

6302510